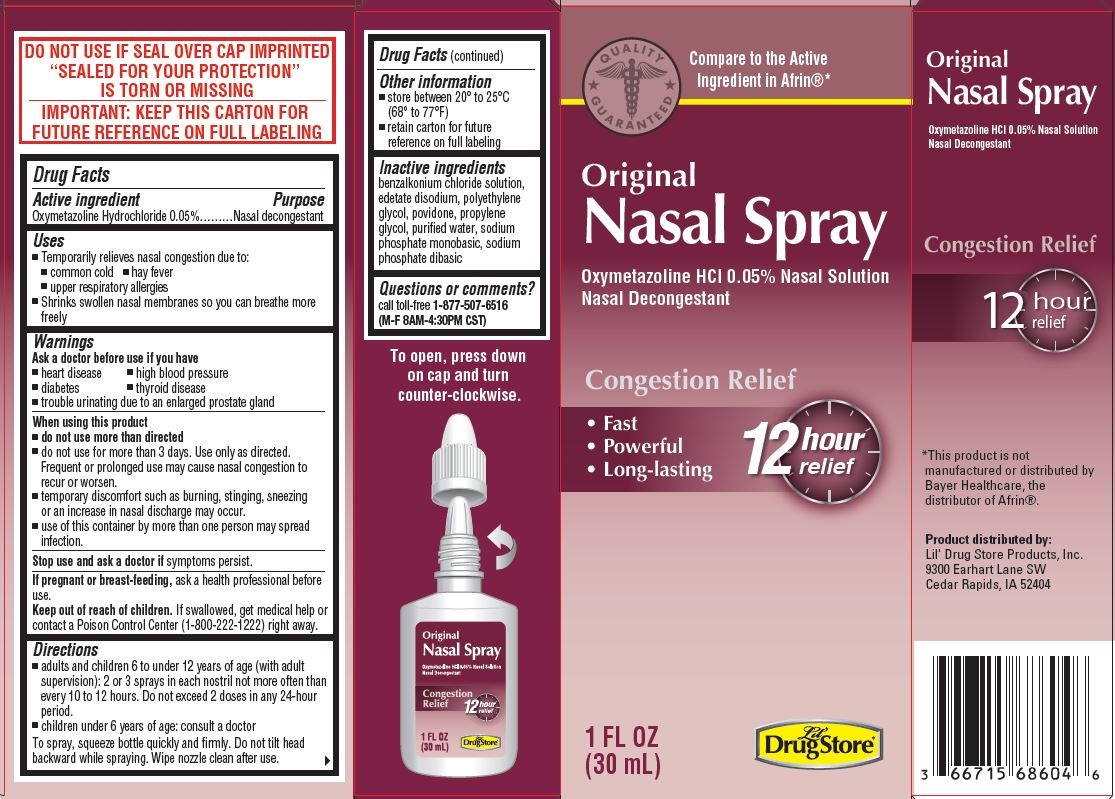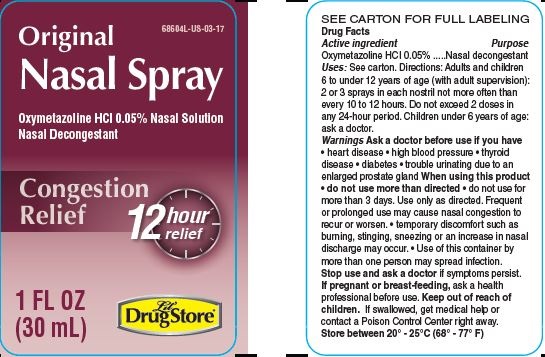 DRUG LABEL: Congestion Relief
NDC: 66715-6860 | Form: SPRAY
Manufacturer: Lil' Drug Store Products, Inc
Category: otc | Type: HUMAN OTC DRUG LABEL
Date: 20241231

ACTIVE INGREDIENTS: OXYMETAZOLINE HYDROCHLORIDE 0.05 g/100 mL
INACTIVE INGREDIENTS: BENZALKONIUM CHLORIDE; EDETATE DISODIUM; GLYCERIN; POLYETHYLENE GLYCOL, UNSPECIFIED; POVIDONE, UNSPECIFIED; PROPYLENE GLYCOL; WATER; SODIUM PHOSPHATE, MONOBASIC, UNSPECIFIED FORM; SODIUM PHOSPHATE, DIBASIC, UNSPECIFIED FORM

Nasal Spray Congestion Relief
Lil' Drug Store® Products

Drug Facts

Active ingredient

Oxymetazoline Hydrochloride 0.05%

Purpose

Nasal decongestant

Uses

- Temporarily relieves nasal congestion due to:
  - common cold
  - hay fever
  - upper respiratory allergies
- Shrinks swollen nasal membranes so you can breathe more freely

Warnings

Ask a doctor before use if you have

- heart disease
- high blood pressure
- diabetes
- thyroid disease
- trouble urinating due to an enlarged prostate gland

When using this product

- do not use more than directed
- do not use for more than 3 days. Use only as directed. Frequent or prolonged use may cause nasal congestion to recur or worsen.
- temporary discomfort such as burning, stinging, sneezing or an increase in nasal discharge may occur.
- use of this container by more than one person may spread infection.

Stop use and ask a doctor if symptoms persist.

PREGNANCY OR BREAST FEEDING

If pregnant or breast-feeding, ask a health professional before use.

Keep out of reach of children. If swallowed, get medical help or contact a Poison Control Center (1-800-222-1222) right away.

Directions

- adults and children 6 to under 12 years of age (with adult supervision): 2 or 3 sprays in each nostril not more often than every 10 to 12 hours. Do not exceed 2 doses in any 24-hour period.
- children under 6 years of age: consult a doctor

To spray, squeeze bottle quickly and firmly. Do not tilt head backward while spraying. Wipe nozzle clean after use.

Other information

- store between 20° to 25°C (68° to 77°F)
- retain carton for future reference on full labeling

Inactive ingredients

benzalkonium chloride solution, edetate disodium, polyethylene glycol, povidone, propylene glycol, purified water, sodium phosphate monobasic, sodium phosphate dibasic

Questions or comments

call toll-free 1-877-507-6516 (M-F 8AM-4:30PM CST)

Product distributed by:
Lil' Drug Store Products, Inc.
9300 Earhart Lane SW
Cedar Rapids, IA 52404

PRINCIPAL DISPLAY PANEL - 30 mL Bottle Carton

QUALITY
⋆GUARANTEED⋆

Compare to the Active
Ingredient in Afrin®*

Original
Nasal Spray

Oxymetazoline HCl 0.05% Nasal Solution
Nasal Decongestant

Congestion Relief

- Fast
- Powerful
- Long-lasting

12 hour
relief

1 FL OZ
(30 mL)

Lil'
Drug Store®